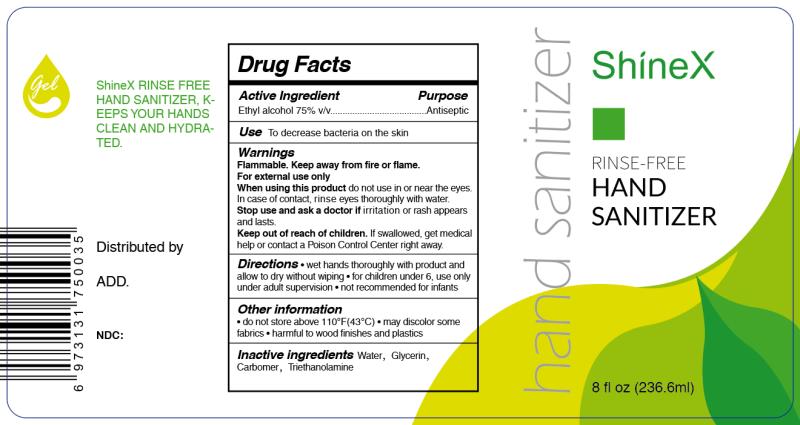 DRUG LABEL: hand sanitizer
NDC: 75230-003 | Form: GEL
Manufacturer: Zhejiang Hongshiliang Health Technology Co., Ltd.
Category: otc | Type: HUMAN OTC DRUG LABEL
Date: 20200507

ACTIVE INGREDIENTS: ALCOHOL 75 mL/100 mL
INACTIVE INGREDIENTS: WATER; GLYCERIN; CARBOMER 934; TROLAMINE

75230-003 Hand Sanitizer

Active Ingredient

Ethyl Alcohol 75%

Purpose

Antiseptic

Use

Use To decrease bacteria on the skin

WARNINGS

Flammable. Keep away from fire or flame.
For external use only
When using this product do not use in or near the
eyes. In case of contact, rinse eyes thoroughly with
water. Stop use and ask a doctor if irritation or
rash appears and lasts.

keep out of reach of children

If swallowed, get medical help
or contact a Poison Control Center right away.

Directions

Directions●wet hands thoroughly with product
and allow to dry without wiping●for children under 6,
use only under adult supervision●not recommended
for infants
Other information
●do not store above 110°F(43°C)
●may discolor some fabrics
●harmful to wood finishes and plastics

Inactive ingredients

Water, ,Glycerin,Carbomer,Triethanolamine